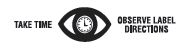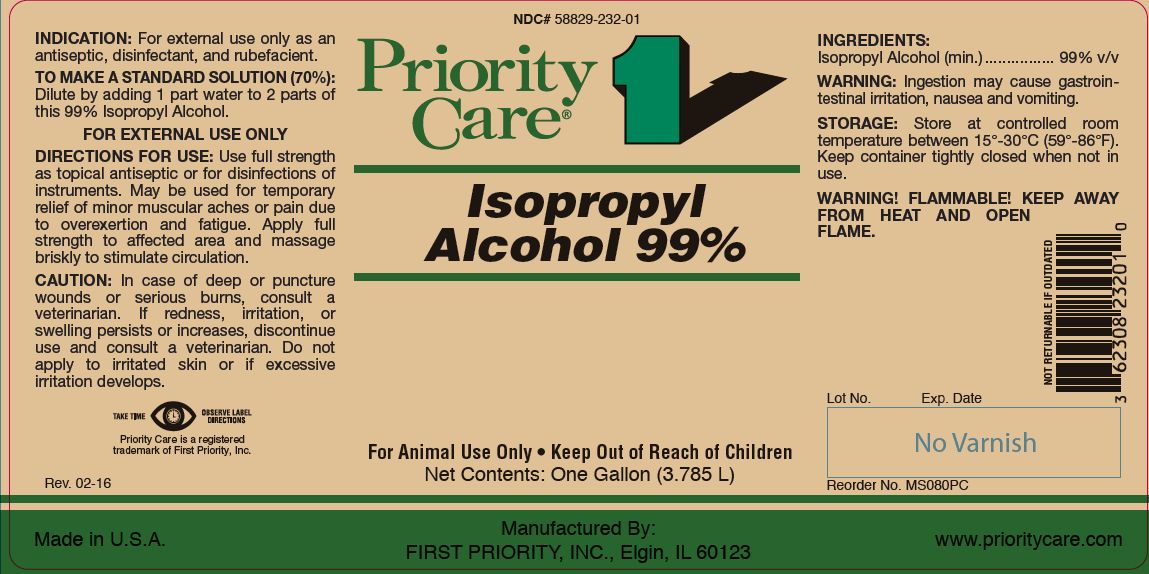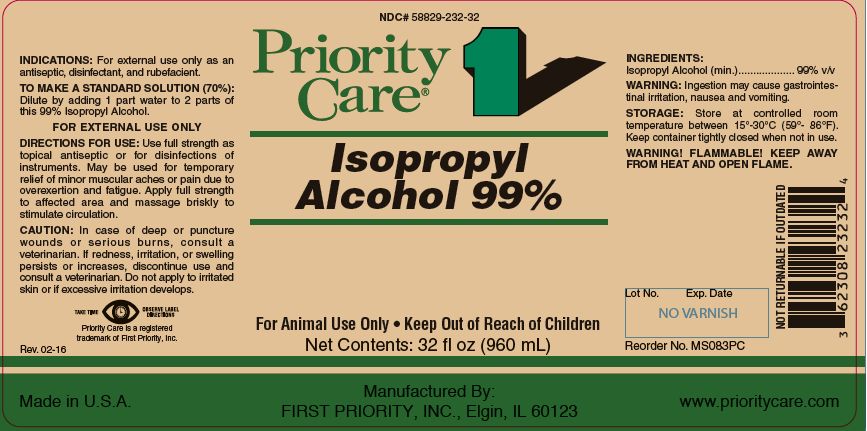 DRUG LABEL: Isopropyl Alcohol
NDC: 58829-232 | Form: LIQUID
Manufacturer: FIRST PRIORITY INCORPORATED
Category: animal | Type: OTC ANIMAL DRUG LABEL
Date: 20241028

ACTIVE INGREDIENTS: ISOPROPYL ALCOHOL 785 g/1 L

ISOPROPYL ALCOHOL 99%

KEEP OUT OF REACH OF CHILDREN

For Animal Use Only
Keep Out of Reach of Children

INDICATIONS:

For external use only as an antiseptic, disinfectant, and rubefacient.

TO MAKE A STANDARD SOLUTION (70%):

Dilute by adding 1 part water to 2 parts of this 99% Isopropyl Alcohol.
FOR EXTERNAL USE ONLY

DIRECTIONS FOR USE:

Use full strength as a topical antiseptic or for the disinfection of instruments. May be used for temporary relief of minor muscular aches or pain due to overexertion and fatigue. Apply full strength to affected area and massage briskly to stimulate circulation.

CAUTION:

In case of deep or puncture wounds or serious burns, consult a veterinarian. If redness, irritation, or swelling persists or increases, discontinue use and consult a veterinarian. Do not apply to irritated skin or if excessive irritation develops.

INGREDIENTS:

Isopropyl Alcohol (min.) .................. 99% v/v

WARNING:

Ingestion may cause gastrointestinal irritation, nausea and vomiting.

STORAGE:

Store at controlled room temperature between 15º to 30ºC (59º-86ºF). Keep container tightly closed when not in use.
WARNING! FLAMMABLE! KEEP AWAY FROM HEAT AND OPEN FLAME.

Net Contents:

32 fl oz (960 mL) Reorder No. MS083PC

One Gallon (3.785 L) Reorder No. MS080PC

INFORMATION FOR OWNERS/CAREGIVERS

Priority Care is a registered trademark of First Priority, Inc.

Made in U.S.A.

Manufactured By: FIRST PRIORITY, INC., Elgin, IL 60123

www.prioritycare.com

NOT RETURNABLE IF OUTDATED